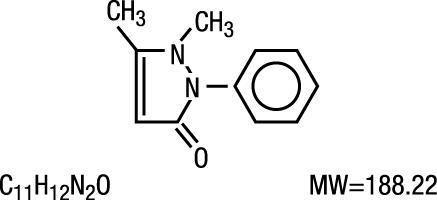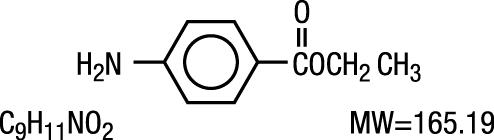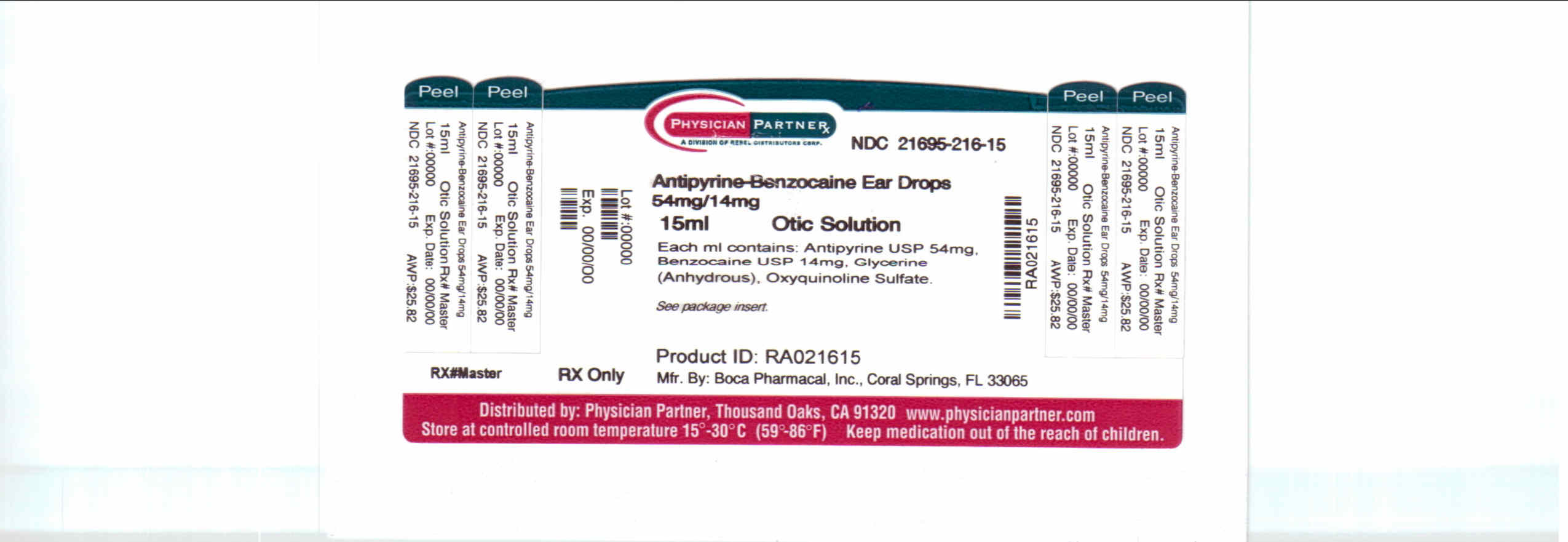 DRUG LABEL: Antipyrine and Benzocaine
NDC: 21695-216 | Form: SOLUTION
Manufacturer: Rebel Distributors Corp
Category: prescription | Type: HUMAN PRESCRIPTION DRUG LABEL
Date: 20110117

ACTIVE INGREDIENTS: ANTIPYRINE 54 mg/1 mL; BENZOCAINE 14 mg/1 mL
INACTIVE INGREDIENTS: GLYCERIN; OXYQUINOLINE SULFATE

ANTIPYRINE AND BENZOCAINE OTIC SOLUTION

DESCRIPTION

Antipyrine and Benzocaine Otic Solution is an otic solution containing Antipyrine, Benzocaine, Oxyquinoline Sulfate, and Anhydrous Glycerin for use in the ear. The solution congeals at 0°C (32°F), but returns to normal consistency, unchanged, at room temperature.

Antipyrine is an analgesic with local anesthetic action, it is chemically 2,3-dimethyl-1-phenyl-3-pyrazolin-5- one.
The active ingredient is represented by the structural formula:

Antipyrine occurs as colorless crystals or white powder, has a slightly bitter taste and is soluble in water and alcohol.

Benzocaine is a local anesthetic. It is chemically ethyl p-aminobenzoate or Benzoic acid, 4-amino-, ethyl ester.
The active ingredient is represented by the structural formula:

It occurs as white crystals or white crystalline powder and is slightly soluble in water and soluble in organic solvents.

EACH mL CONTAINS:

Actives: Antipyrine 54 mg, Benzocaine 14 mg; Inactives: Glycerine (anhydrous), Oxyquinoline Sulfate.

CLINICAL PHARMACOLOGY

Antipyrine and Benzocaine Otic Solution combines the hygroscopic property of anhydrous glycerin with the analgesic action of antipyrine and benzocaine to relieve pressure, reduce inflammation and congestion, and to alleviate pain and discomfort in acute otitis media.

Antipyrine and Benzocaine Otic Solution does not blanch the tympanic membrane or mask the landmarks and, therefore, does not distort the otoscopic picture.

INDICATIONS AND USAGE

Acute Otitis media of various etiologies

-prompt relief of pain and reduction of inflammation in the congestive and serous stages.

-adjuvant therapy during systemic antibiotic administration for resolution of the infection.

Because of the close anatomical relationship of the eustachian tube to the nasal cavity, otitis media is a frequent problem, especially in children in whom the tube is shorter, wider, and more horizontal than in adults.

Removal of Cerumen

-facilitates the removal of excessive or impacted cerumen.

CONTRAINDICATIONS

The product is contraindicated in any person with hypersensitivity to any of the components or substances related to them.
This product is contraindicated in the presence of spontaneous perforation of the tympanic membrane or discharge.

WARNINGS

FOR USE IN EARS ONLY-NOT FOR USE IN EYES

Discontinue promptly if sensitization or irritation occurs.

PRECAUTIONS

Information for Patients: Avoid contaminating the dropper with material from the ear, fingers or other source.

Carcinogenesis, Mutagenesis, Impairment of Fertility

No long term studies have been conducted.

Pregnancy

Pregnancy: Category C. Animal reproduction studies have not been conducted with Antipyrine and Benzocaine Otic Solution.
It is also not known whether Antipyrine and Benzocaine Otic Solution can cause fetal harm when administered to a pregnant woman or can affect reproduction capacity. Antipyrine and Benzocaine
Otic Solution should be given to a pregnant woman only if clearly needed.

Nursing Mothers

It is not known whether this drug is excreted in human milk. Because many drugs are excreted in human milk, caution should be exercised when Antipyrine and Benzocaine Otic Solution is administered to a nursing woman.

DOSAGE AND ADMINISTRATION

Acute otitis media: Instill Antipyrine and Benzocaine Otic Solution, permitting the solution to run along the wall of the ear canal until it is filled. Avoid touching the ear with dropper. Then moisten a cotton pledget with Antipyrine and Benzocaine Otic Solution and insert into meatus. Repeat every one to two hours until pain and congestion are relieved.

Removal of Cerumen:

Before: Instill Antipyrine and Benzocaine Otic Solution three times daily for two or three days to help detach cerumen from wall of ear canal and facilitate removal.

After: Antipyrine and Benzocaine Otic Solution is useful for drying out the ear canal or relieving discomfort.

Before and after removal of cerumen, a cotton pledget moistened with Antipyrine and Benzocaine Otic Solution should be inserted into the meatus following instillation.

HOW SUPPLIED

Antipyrine and Benzocaine Otic Solution NDC 21695-216-15 is supplied in a 15 mL light-resistant dropper-bottle with a screwtop bottle cap. Tamper evident seal on bottle cap. Do not use if seal is broken.

Storage and Handling

Store at 20°-25°C (68°-77°F) [see USP Controlled Room Temperature]. Protect from heat and light. Protect from freezing.

Call your doctor for medical advice about side effects. You may report side effects to the FDA at 1-800-FDA-1088.

Manufactured for:

Boca Pharmacal, Inc.

Coral Springs, FL 33065

www.bocapharmacal.com

1-800-354-8460

Rev. 04/09

Repackaged by:

Rebel Distributors Corp

Thousand Oaks, CA 91320